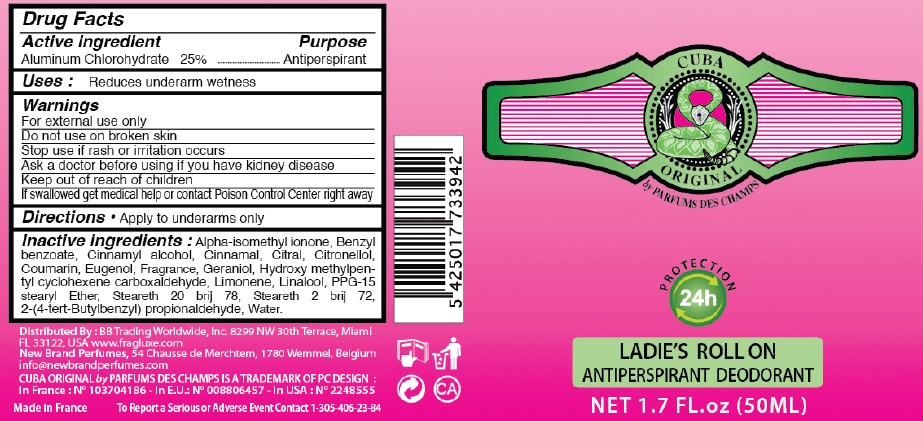 DRUG LABEL: CUBA ORIGINAL LADIES ROLL ON ANTIPERSPIRANT DEODORANT
NDC: 49902-3942 | Form: LIQUID
Manufacturer: BB TRADING WORLDWIDE, INC
Category: otc | Type: HUMAN OTC DRUG LABEL
Date: 20110118

ACTIVE INGREDIENTS: ALUMINUM CHLOROHYDRATE 25 mL/100 mL
INACTIVE INGREDIENTS: IONONE; BENZYL BENZOATE; CINNAMYL ALCOHOL; CITRAL; .BETA.-CITRONELLOL, (R)-; COUMARIN; EUGENOL; GERANIOL; LINALOOL, DL-; WATER

CUBA ORIGINAL BY PARFUMS DES CHAMPS LADIES ROLL ON ANTIPERSPIRANT DEODORANT

DRUG FACTS

Active Ingredient Purpose

Aluminum chlorohydrate 25% Antiperspirant

Purpose:
Antiperspirant

INDICATIONS AND USAGE

Uses: Reduces underarm wetness

WARNINGS

For external use only. Do not use on broken skin.

Stop use if rash or irritation occurs.

Ask a doctor before using if you have kidney disease.

Keep out of reach of children. If swallowed get medical help or contact Poison Control Center right away.

Directions

Apply to underarms only

Inactive Ingredients

Alpha-isomethyl ionone, Benxyl benzoate, Cinnamyl alcohol, cinnamal, citral, citronellol, coumarin, eugenol, fragrance, geraniol, hydroxy methylpentyl cyclohexane carboxaldehyde, Limonene, Linalool, PPG-15 stearyl Ether, Steareth 20 brij 78, Steareth 2 brij 72, 2-(4-tert butylbenzyl)propionaldehyde, water

Distributed by: BB Trading Worldwide, Inc. 8299 NW 30th Terrace, Miami FL 33122, USA, www.fragluxe.com

Newbrand perfumes, 54 Chausse de Merchtem, 1780 Wemmel, Belgium

info@newbrandperfumes.com

CUBA ORIGINAL BY PARFUMS DES CHAMPS IS A TRADEMARK OF PC DESIGN

in France: No 103704186

In E.U.: 008806457

In USA No 2248555

Made in France

To report a Serious or Adverse Event Contact 1-305-406-23-84

PACKAGE LABEL

CUBA ORIGINAL
by PARFUMS DES CHAMPS
PROTECTION 24H
LADIES ROLLON
ANTIPERSPIRANT DEODORANT
NET 1.7 FL OZ (50ML)